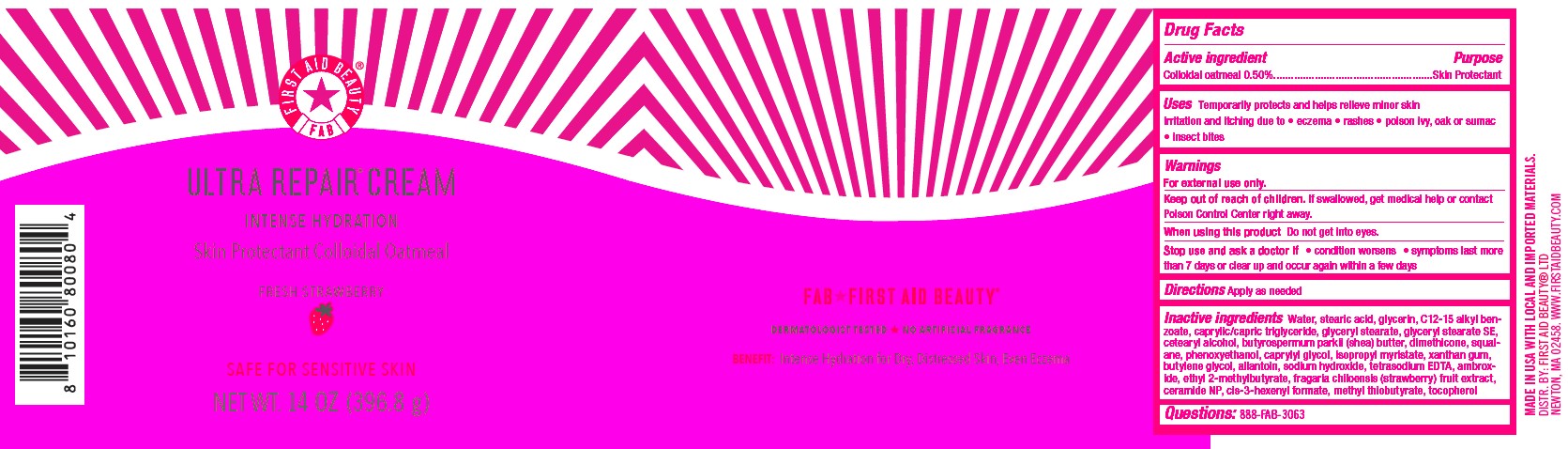 DRUG LABEL: First Aid Beauty FAB Ultra Repair Cream Intense Hydration Skin Protectant Fresh Strawberry
NDC: 84126-105 | Form: CREAM
Manufacturer: The Procter & Gamble Manufacturing Company
Category: otc | Type: HUMAN OTC DRUG LABEL
Date: 20250319

ACTIVE INGREDIENTS: OATMEAL 0.5 g/100 g
INACTIVE INGREDIENTS: SQUALANE; BUTYLENE GLYCOL; 3-HEXEN-1-OL, FORMATE, (Z)-; GLYCERYL STEARATE SE; METHYL THIOBUTYRATE; CETEARYL ALCOHOL; DIMETHICONE; TETRASODIUM EDTA; C12-15 ALKYL BENZOATE; CAPRYLYL GLYCOL; SODIUM HYDROXIDE; PHENOXYETHANOL; BUTYROSPERMUM PARKII (SHEA) BUTTER; WATER; GLYCERIN; ALLANTOIN; GLYCERYL STEARATE; CAPRYLIC/CAPRIC TRIGLYCERIDE; STEARIC ACID; XANTHAN GUM; CERAMIDE NP; BEACH STRAWBERRY; AMAROLIDE; ETHYL 2-METHYLBUTYRATE; METHYL PHENYLACETATE; ISOPROPYL MYRISTATE; TOCOPHEROL

First Aid Beauty FAB Ultra Repair Cream Skin Protectant Vanilla Cinnamon

Drug Facts

Active ingredients

Colloidal Oatmeal 0.5%

Purpose

Skin Protectant

Uses

- Temporarily protects and helps relieve minor skin irritation and itching due to eczema, rashes, poison ivy, oak or sumac, insect bites

Warnings

For external use only.

Keep out of reach of children. If swallowed, get medical help or contact a Poison Control Center right away.

WHEN USING

Do not get into eyes.

Stop use and ask a doctor if condition worsens, symptoms last more than 7 days or clear up and occur again within a few days

Directions

Apply as needed

INACTIVE INGREDIENT

Water, stearic acid, glycerin, C12-15 alkyl benzoate, caprylic/capric triglyceride, glyceryl stearate, glyceryl stearate SE, cetearyl alcohol, butyrospermum parkii (shea) butter, dimethicone, squalane, phenoxyethanol, caprylyl glycol, isopropyl myristate, xanthan gum, butylene glycol, allantoin, sodium hydroxide, tetrasodium EDTA, ambroxide, ethyl 2-methylbutyrate, fragaria chiloensis (strawberry) fruit extract, ceramide NP, cis-3-hexenyl formate, methyl thiobutyrate, tocopherol

Questions:

888-FAB-3063

MADE IN USA

FIRST AID BEAUTY LTD

NEWTON, MA 02458

WWW.FIRSTAIDBEAUTY.COM

PRINCIPAL DISPLAY PANEL - 396.8 g (14 oz)

First Aid Beauty

FAB

Ultra Repair® Cream

Intense Hydration

Skin Protectant Colloidal Oatmeal

FRESH STRAWBERRY

Net Wt. 396.8 g (14 oz)